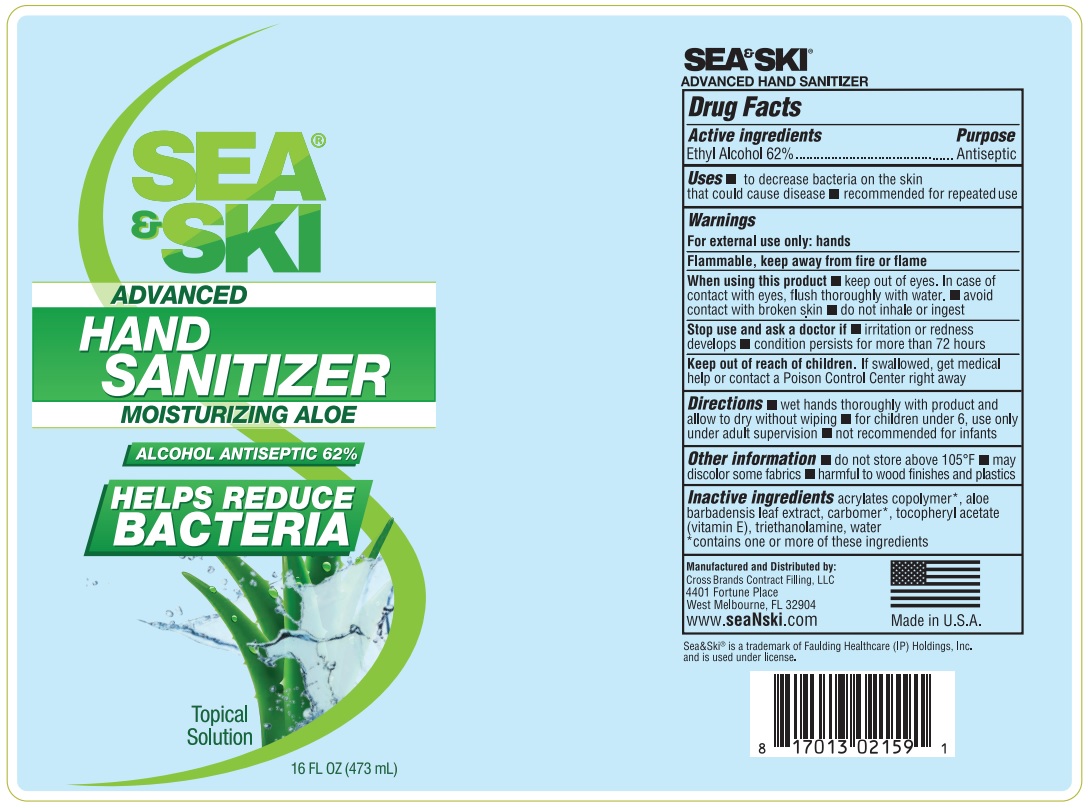 DRUG LABEL: Sea and Ski Hand Sanitizer Gel
NDC: 73440-2159 | Form: GEL
Manufacturer: Cross Brands Contract Filling
Category: otc | Type: HUMAN OTC DRUG LABEL
Date: 20210219

ACTIVE INGREDIENTS: ALCOHOL 258.07 g/416.24 g
INACTIVE INGREDIENTS: WATER 131.55 g/416.24 g

Sea & Ski Advance Hand Sanitizer Gel 16oz

Active Ingredient

Ethyl Alcohol 62%

Purpose

Antiseptic

Uses

To decrease bacteria on the skin that could cause disease

Recommended for repeated use

Warnings

For external use only: Hands

Flammable, keep away from fire or flame

When Using

When using this product keep out of eyes. In case of contact with eyes, flush thoroughly with water. Avoid contact with broken skin. Do not inhale or ingest

Stop use

Stop Use and ask a doctor if irritation or redness develops condition persists for more than 72 hours

Keep out of reach of children. If swallowed, get medical help or contact a Poison Control Center right away.

Directions

wet hands thoroughly with product and allow to dry without wiping for children under 6, use only under adult supervision not recommended for infants

Other information

do not store above 105°F may discolor some fabrics harmful to wood finishes and plastics

Inactive Ingredients

acrylates copolymer*, aloe barbadensis leaf extract carbomer*, tocopheryl acetate (vitamin E), triethanolamine, water

*contains one or more of these ingredients